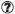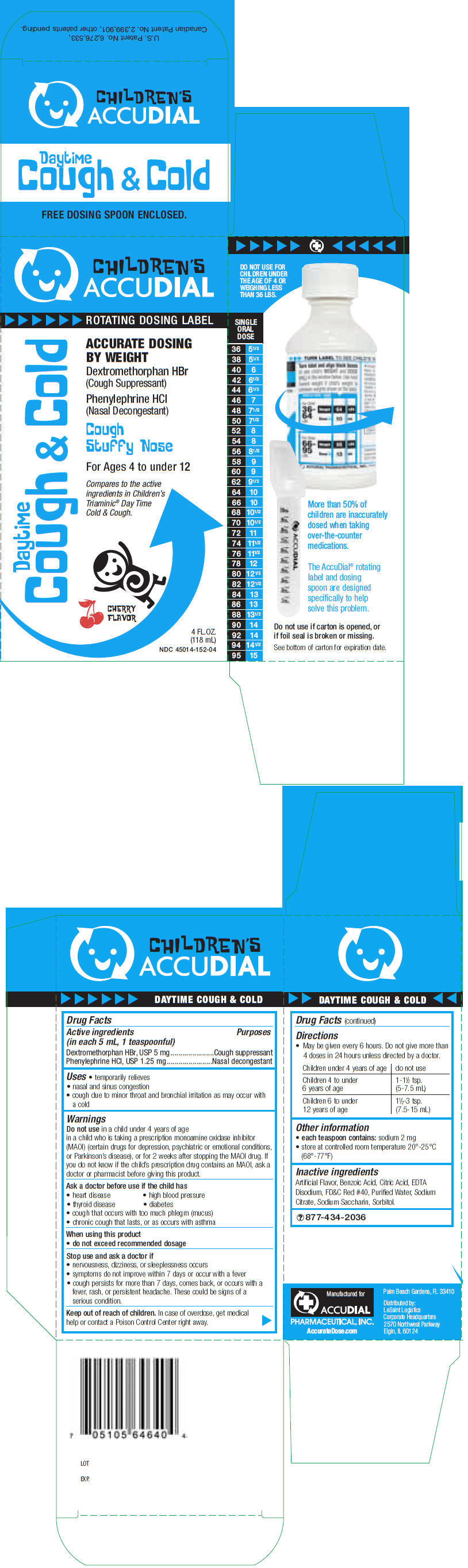 DRUG LABEL: Daytime Cough And Cold
NDC: 45014-152 | Form: LIQUID
Manufacturer: Accudial Pharmaceutical, Inc.
Category: otc | Type: HUMAN OTC DRUG LABEL
Date: 20110928

ACTIVE INGREDIENTS: Dextromethorphan Hydrobromide 5 mg/5 mL; Phenylephrine Hydrochloride 1.25 mg/5 mL
INACTIVE INGREDIENTS: Cherry; Benzoic acid; Citric Acid Monohydrate; Edetate Disodium; FD&C red no. 40; Propylene Glycol; Water; Sodium Citrate; Saccharin Sodium; Sorbitol

Drug Facts

ACTIVE INGREDIENT

PURPOSE

Active ingredients (in each 5 mL, 1 teaspoonful) | Purposes
Dextromethorphan HBr, USP 5 mg | Cough suppressant
Phenylephrine HCl, USP 1.25 mg | Nasal decongestant

Uses

- temporarily relieves
  - nasal and sinus congestion
  - cough due to minor throat and bronchial irritation as may occur with a cold

Warnings

Do not use in a child under 4 years of age

in a child who is taking a prescription monoamine oxidase inhibitor (MAOI) (certain drugs for depression, psychiatric or emotional conditions, or Parkinson's disease), or for 2 weeks after stopping the MAOI drug. If you do not know if the child's prescription drug contains an MAOI, ask a doctor or pharmacist before giving this product.

Ask a doctor before use if the child has

- heart disease
- high blood pressure
- thyroid disease
- diabetes
- cough that occurs with too much phlegm (mucus)
- chronic cough that lasts, or as occurs with asthma

When using this product

- do not exceed recommended dosage

Stop use and ask a doctor if

- nervousness, dizziness, or sleeplessness occurs
- symptoms do not improve within 7 days or occur with a fever
- cough persists for more than 7 days, comes back, or occurs with a fever, rash, or persistent headache. These could be signs of a serious condition.

Keep out of reach of children. In case of overdose, get medical help or contact a Poison Control Center right away.

Directions

- May be given every 6 hours. Do not give more than 4 doses in 24 hours unless directed by a doctor.

Children under 4 years of age | do not use
Children 4 to under 6 years of age | 1-1½ tsp. (5-7.5 mL)
Children 6 to under 12 years of age | 1½-3 tsp. (7.5-15 mL)

Other information

- each teaspoon contains: sodium 2 mg
- store at controlled room temperature 20°-25°C (68°-77°F)

Inactive ingredients

Artificial Flavor, Benzoic Acid, Citric Acid, EDTA Disodium, FD&C Red #40, Purified Water, Sodium Citrate, Sodium Saccharin, Sorbitol.

QUESTIONS

877-434-2036

Manufactured for
ACCUDIAL
PHARMACEUTICAL, INC.
AccurateDose.com
Palm Beach Gardens, FL 33410

Distributed by:
LeSaint Logistics
Corporate Headquarters
2570 Northwest Parkway
Elgin, IL 60124

PRINCIPAL DISPLAY PANEL - 118 mL Bottle Carton

CHILDREN'S
ACCUDIAL

ROTATING DOSING LABEL

Daytime
Cough & Cold

ACCURATE DOSING
BY WEIGHT

Dextromethorphan HBr
(Cough Suppressant)

Phenylephrine HCl
(Nasal Decongestant)

Cough
Stuffy Nose

For Ages 4 to under 12

Compares to the active
ingredients in Children's
Triaminic® Day Time
Cold & Cough.

CHERRY
FLAVOR

4 FL.OZ.
(118 mL)

NDC 45014-152-04